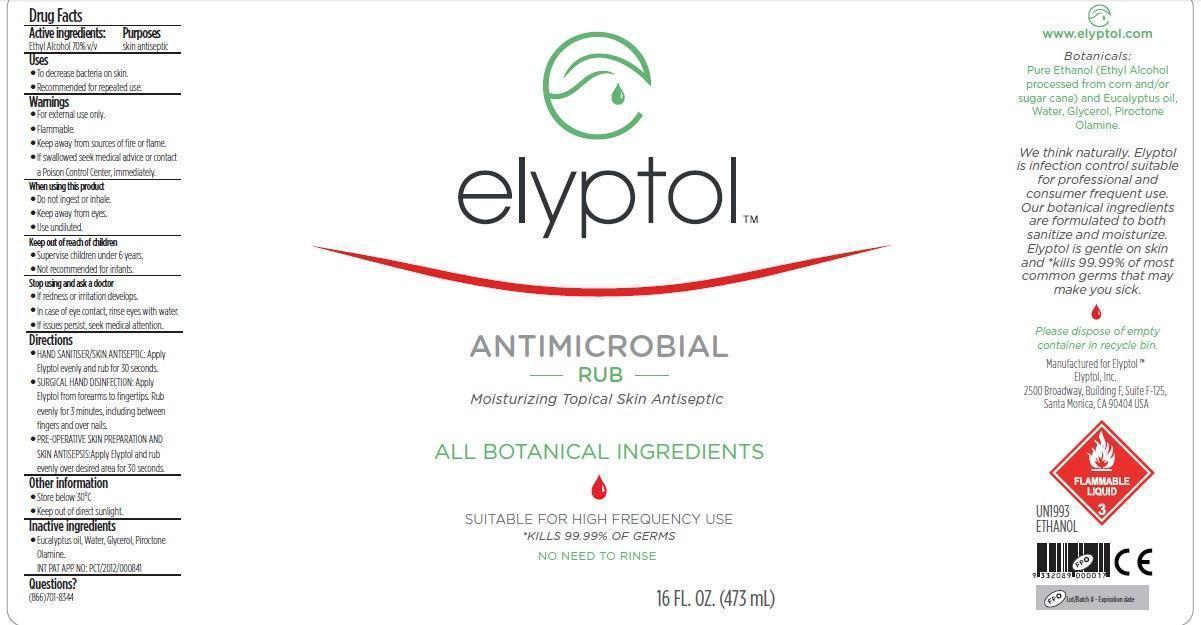 DRUG LABEL: Elyptol Antimicrobial Rub
NDC: 69343-221 | Form: SOLUTION
Manufacturer: Elyptol Inc.
Category: otc | Type: HUMAN OTC DRUG LABEL
Date: 20221219

ACTIVE INGREDIENTS: ALCOHOL 7 mL/10 mL
INACTIVE INGREDIENTS: EUCALYPTUS OIL; WATER; GLYCERIN; PIROCTONE OLAMINE

Elyptol Antimicrobial Rub

Active ingredients:

Ethyl Alcohol 70% v/v

Purpose

Skin antiseptic

Keep out reach of children

- Supervise children under 6 years.
- Not recommended for infants.

Uses

- To decrease bacteria on skin.
- Recommended for repeated use.

Warnings

- For external use only

Flammable.

- Keep away from sources of fire or flame.
- If swallowed seek medical advice or contact a Poison Control Center, immediately.

When using this product

- Do not ingest or inhale.
- Keep away from eyes.
- Use undiluted.

Stop using and ask a doctor

- If redness or irritation develops.
- In case of eye contact, rinse eyes with water.
- If issues persist, seek medical attention.

Directions

• HAND SANITISER/SKIN ANTISEPTIC: Apply Elyptol evenly and rub for 30 seconds.
• SURGICAL HAND DISINFECTION: Apply Elyptol from forearms to fingertips. Rub evenly for 3 minutes, including between fingers and over nails.
• PRE-OPERATIVE SKIN PREPARATION AND SKIN ANTISEPSIS: Apply Elyptol and rub evenly over desired area for 30 seconds.

Other Information

Store below 30°C
Keep out of direct sunlight.

Inactive ingredients

Eucalyptus oil, Water, Glycerol, Cellulose, Piroctone Olamine.

INT PAT APP NO: PCT/2012/000841

Questions?

(866)701-8344